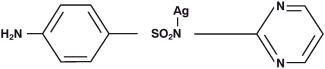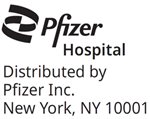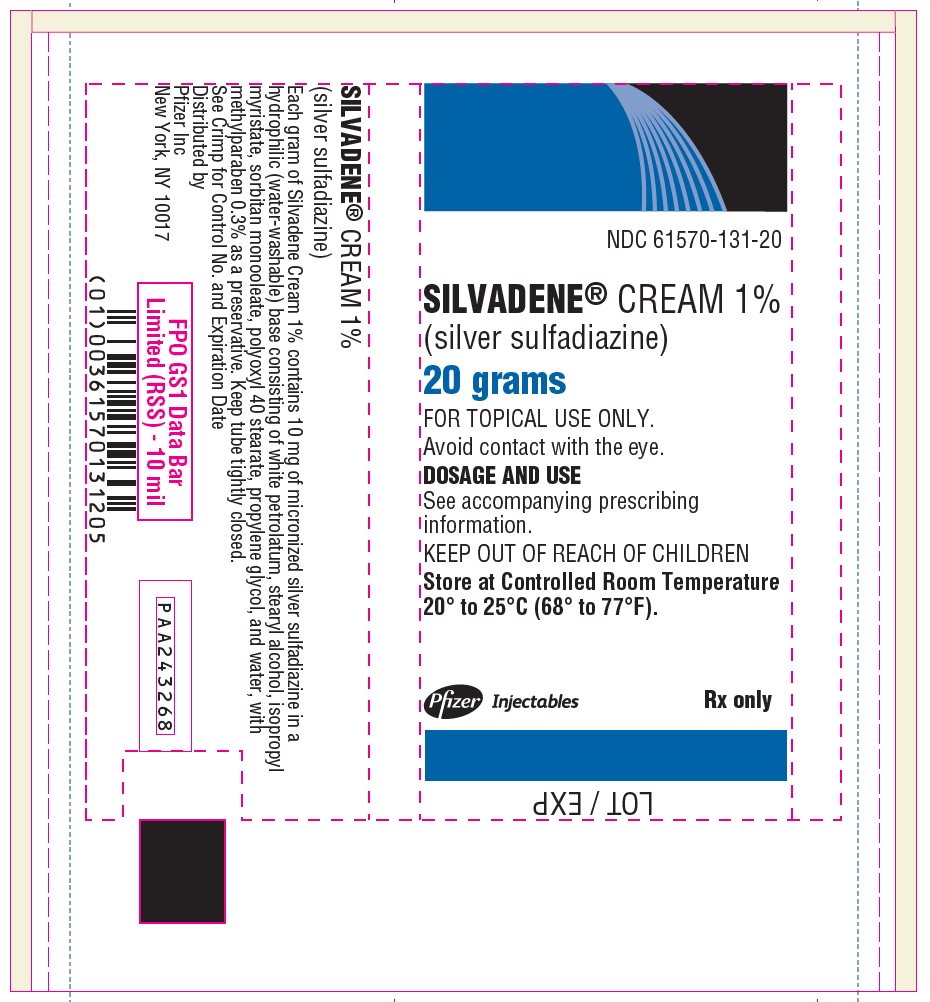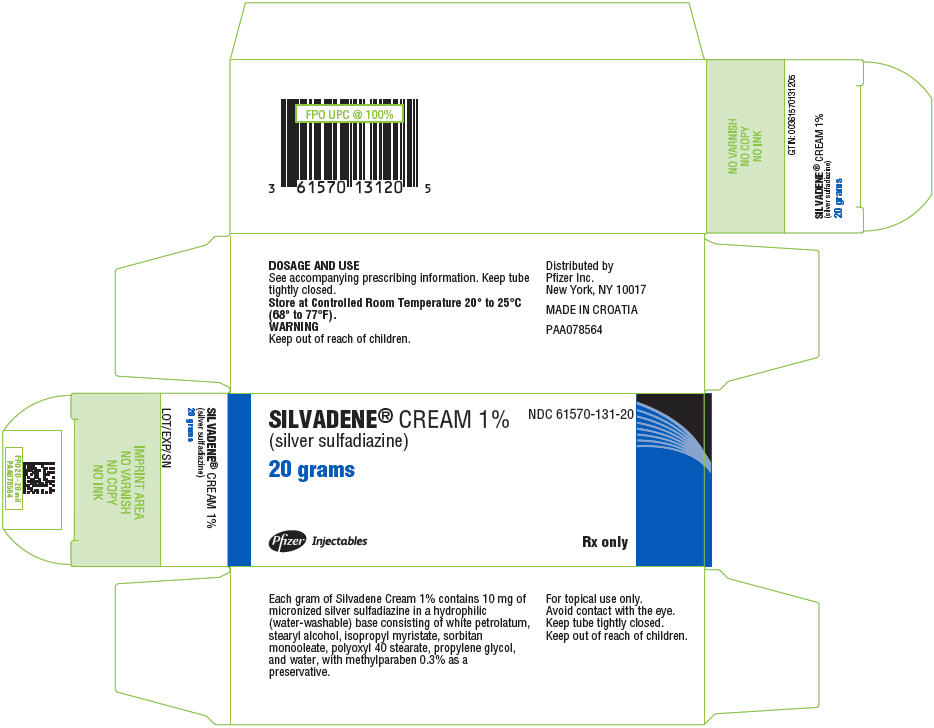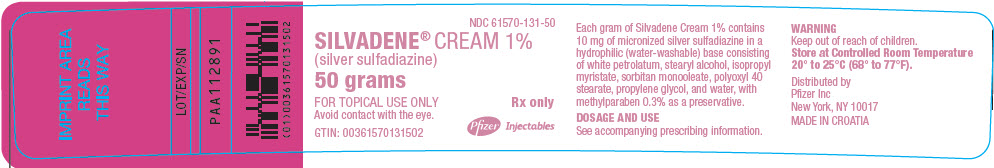 DRUG LABEL: SILVADENE
NDC: 61570-131 | Form: CREAM
Manufacturer: Pfizer Laboratories Div Pfizer Inc
Category: prescription | Type: HUMAN PRESCRIPTION DRUG LABEL
Date: 20260126

ACTIVE INGREDIENTS: SILVER SULFADIAZINE 10 mg/1 g

SILVADENE® CREAM 1%
(silver sulfadiazine)

DESCRIPTION

SILVADENE Cream 1% is a soft, white, water-miscible cream containing the antimicrobial agent silver sulfadiazine in micronized form, which has the following structural formula:

Each gram of SILVADENE Cream 1% contains 10 mg of micronized silver sulfadiazine. The cream vehicle consists of white petrolatum, stearyl alcohol, isopropyl myristate, sorbitan monooleate, polyoxyl 40 stearate, propylene glycol, and water, with methylparaben 0.3% as a preservative. SILVADENE Cream 1% (silver sulfadiazine) spreads easily and can be washed off readily with water.

CLINICAL PHARMACOLOGY

Silver sulfadiazine has broad antimicrobial activity. It is bactericidal for many gram-negative and gram-positive bacteria as well as being effective against yeast. Results from in vitro testing are listed below.

Sufficient data have been obtained to demonstrate that silver sulfadiazine will inhibit bacteria that are resistant to other antimicrobial agents and that the compound is superior to sulfadiazine.

Studies utilizing radioactive micronized silver sulfadiazine, electron microscopy, and biochemical techniques have revealed that the mechanism of action of silver sulfadiazine on bacteria differs from silver nitrate and sodium sulfadiazine. Silver sulfadiazine acts only on the cell membrane and cell wall to produce its bactericidal effect.

Results of In Vitro Testing with SILVADENE® Cream 1% (silver sulfadiazine) Concentration of Silver Sulfadiazine Number of Sensitive Strains/Total Number of Strains Tested
Genus & Species | 50 μg/mL | 100 μg/mL
Pseudomonas
aeruginosa | 130/130 | 130/130
Xanthomonas (Pseudomonas)
maltophilia | 7/7 | 7/7
Enterobacter species | 48/50 | 50/50
Enterobacter cloacae | 24/24 | 24/24
Klebsiella species | 53/54 | 54/54
Escherichia coli | 63/63 | 63/63
Serratia species | 27/28 | 28/28
Proteus mirabilis | 53/53 | 53/53
Morganella morganii | 10/10 | 10/10
Providencia rettgeri | 2/2 | 2/2
Providencia species | 1/1 | 1/1
Proteus vulgaris | 2/2 | 2/2
Citrobacter species | 10/10 | 10/10
Acinetobacter
calcoaceticus | 10/11 | 11/11
Staphylococcus aureus | 100/101 | 100/101
Staphylococcus
epidermidis | 51/51 | 51/51
β-Hemolytic
Streptococcus | 4/4 | 4/4
Enterococcus species | 52/53 | 53/53
Corynebacterium-
diphtheriae | 2/2 | 2/2
Clostridium perfringens | 0/2 | 2/2
Candida albicans | 43/50 | 50/50

Silver sulfadiazine is not a carbonic anhydrase inhibitor and may be useful in situations where such agents are contraindicated.

INDICATIONS AND USAGE

SILVADENE Cream 1% (silver sulfadiazine) is a topical antimicrobial drug indicated as an adjunct for the prevention and treatment of wound sepsis in patients with second- and third-degree burns.

CONTRAINDICATIONS

SILVADENE Cream 1% (silver sulfadiazine) is contraindicated in patients who are hypersensitive to silver sulfadiazine or any of the other ingredients in the preparation.

Because sulfonamide therapy is known to increase the possibility of kernicterus, SILVADENE Cream 1% should not be used on pregnant women approaching or at term, on premature infants, or on newborn infants during the first 2 months of life.

WARNINGS

Absorption of silver sulfadiazine varies depending upon the percent of body surface area and the extent of the tissue damage. Although few have been reported, it is possible that any adverse reaction associated with sulfonamides may occur. Some of the reactions, which have been associated with sulfonamides, are as follows: blood dyscrasias including agranulocytosis, aplastic anemia, thrombocytopenia, leukopenia, and hemolytic anemia; dermatologic and allergic reactions, including life-threatening cutaneous reactions [Stevens-Johnson syndrome (SJS), toxic epidermal necrolysis (TEN) and exfoliative dermatitis]; gastrointestinal reactions; hepatitis and hepatocellular necrosis; CNS reactions; and toxic nephrosis.

There is potential cross-sensitivity between silver sulfadiazine and other sulfonamides. If allergic reactions attributable to treatment with silver sulfadiazine occur, continuation of therapy must be weighed against the potential hazards of the particular allergic reaction.

Fungal proliferation in and below the eschar may occur. However, the incidence of clinically reported fungal superinfection is low.

The use of SILVADENE Cream 1% (silver sulfadiazine) in some cases of glucose-6-phosphate dehydrogenase-deficient individuals may be hazardous, as hemolysis may occur.

PRECAUTIONS

General

If hepatic and renal functions become impaired and elimination of drug decreases, accumulation may occur, and discontinuation of SILVADENE Cream 1% (silver sulfadiazine) should be weighed against the therapeutic benefit being achieved.

In considering the use of topical proteolytic enzymes in conjunction with SILVADENE Cream 1%, the possibility should be noted that silver may inactivate such enzymes.

SILVADENE Cream 1% (silver sulfadiazine) is for topical use only. Avoid contact of SILVADENE Cream 1% (silver sulfadiazine) with the eye.

Laboratory Tests

In the treatment of burn wounds involving extensive areas of the body, the serum sulfa concentrations may approach adult therapeutic levels (8 mg% to 12 mg%). Therefore, in these patients it would be advisable to monitor serum sulfa concentrations. Renal function should be carefully monitored and the urine should be checked for sulfa crystals. Absorption of the propylene glycol vehicle has been reported to affect serum osmolality, which may affect the interpretation of laboratory tests.

Carcinogenesis, Mutagenesis, Impairment of Fertility

Long-term dermal toxicity studies of 24 months' duration in rats and 18 months' in mice with concentrations of silver sulfadiazine three to ten times the concentration in SILVADENE Cream 1% revealed no evidence of carcinogenicity.

Pregnancy

Teratogenic Effects.

A reproductive study has been performed in rabbits at doses up to three to ten times the concentration of silver sulfadiazine in SILVADENE Cream 1% and has revealed no evidence of harm to the fetus due to silver sulfadiazine. There are, however, no adequate and well-controlled studies in pregnant women. Because animal reproduction studies are not always predictive of human response, this drug should be used during pregnancy only if clearly justified, especially in pregnant women approaching or at term (see CONTRAINDICATIONS).

Nursing Mothers

It is not known whether silver sulfadiazine is excreted in human milk. However, sulfonamides are known to be excreted in human milk, and all sulfonamide derivatives are known to increase the possibility of kernicterus. Because of the possibility for serious adverse reactions in nursing infants from sulfonamides, a decision should be made whether to discontinue nursing or to discontinue the drug, taking into account the importance of the drug to the mother.

Geriatric Use

Of the total number of subjects in clinical studies of SILVADENE Cream 1%, seven percent were 65 years of age and over. No overall differences in safety or effectiveness were observed between these subjects and younger subjects, and other reported clinical experience has not identified differences in responses between the elderly and younger patients, but greater sensitivity of some older individuals cannot be ruled out.

Pediatric Use

Safety and effectiveness in pediatric patients have not been established (see CONTRAINDICATIONS).

ADVERSE REACTIONS

Several cases of transient leukopenia have been reported in patients receiving silver sulfadiazine therapy.^1,2,3 Leukopenia associated with silver sulfadiazine administration is primarily characterized by decreased neutrophil count. Maximal white blood cell depression occurs within 2 to 4 days of initiation of therapy. Rebound to normal leukocyte levels follows onset within 2 to 3 days. Recovery is not influenced by continuation of silver sulfadiazine therapy. An increased incidence of leukopenia has been reported in patients treated concurrently with cimetidine.

Other infrequently occurring events include skin necrosis, erythema multiforme, skin discoloration, burning sensation, rashes, and interstitial nephritis.

Reduction in bacterial growth after application of topical antibacterial agents has been reported to permit spontaneous healing of deep partial-thickness burns by preventing conversion of the partial thickness to full thickness by sepsis. However, reduction in bacterial colonization has caused delayed separation, in some cases necessitating escharotomy in order to prevent contracture.

DOSAGE AND ADMINISTRATION

Prompt institution of appropriate regimens for care of the burned patient is of prime importance and includes the control of shock and pain. The burn wounds are then cleansed and debrided, and SILVADENE Cream 1% (silver sulfadiazine) is applied under sterile conditions. The burn areas should be covered with SILVADENE Cream 1% at all times. The cream should be applied once to twice daily to a thickness of approximately 1/16 inch. Whenever necessary, the cream should be reapplied to any areas from which it has been removed by patient activity. Administration may be accomplished in minimal time because dressings are not required. However, if individual patient requirements make dressings necessary, they may be used.

Reapply immediately after hydrotherapy.

Treatment with SILVADENE Cream 1% should be continued until satisfactory healing has occurred, or until the burn site is ready for grafting. The drug should not be withdrawn from the therapeutic regimen while there remains the possibility of infection except if a significant adverse reaction occurs.

HOW SUPPLIED

SILVADENE Cream 1% (silver sulfadiazine) is available in jars containing 50 g (NDC 61570-131-50), 400 g (NDC 61570-131-40), and 1000 g (NDC 61570-131-98), and tubes containing 20 g (NDC 61570-131-20), 25 g (NDC 61570-131-25), 50 g (NDC 61570-131-55) and 85 g (NDC 61570-131-85).

Store at Controlled Room Temperature 20° to 25°C (68° to 77°F).

REFERENCES

1. Caffee F, Bingham H. Leukopenia and silver sulfadiazine. J Trauma. 1982;22: 586–587.
2. Jarret F, Ellerbe S, Demling R. Acute leukopenia during topical burn therapy with silver sulfadiazine. Amer J Surg. 1978;135:818–819.
3. Kiker RG, Carvajal HF, Micak RP, Larson DL. A controlled study of the effects of silver sulfadiazine on white blood cell counts in burned children. J Trauma. 1977; 17:835–836.

This product's label may have been updated. For current full prescribing information, please visit www.pfizer.com.

LAB-0647-7.0

Revised January 2026

PRINCIPAL DISPLAY PANEL - 20 gram Tube Label

NDC 61570-131-20

SILVADENE® CREAM 1%
(silver sulfadiazine)

20 grams

FOR TOPICAL USE ONLY.

Avoid contact with the eye.

DOSAGE AND USE

See accompanying prescribing
information.

KEEP OUT OF REACH OF CHILDREN

Store at Controlled Room Temperature
20° to 25° (68° to 77°F).

Pfizer Injectables

Rx only

PRINCIPAL DISPLAY PANEL - 20 gram Tube Carton

SILVADENE® CREAM 1%
(silver sulfadiazine)

NDC 61570-131-20

20 grams

Pfizer Injectables

Rx only

PRINCIPAL DISPLAY PANEL - 50 gram Jar Label

NDC 61570-131-50

SILVADENE® CREAM 1%
(silver sulfadiazine)
50 grams

FOR TOPICAL USE ONLY
Avoid contact with the eye.

GTIN: 00361570131502

Rx only

Pfizer Injectables